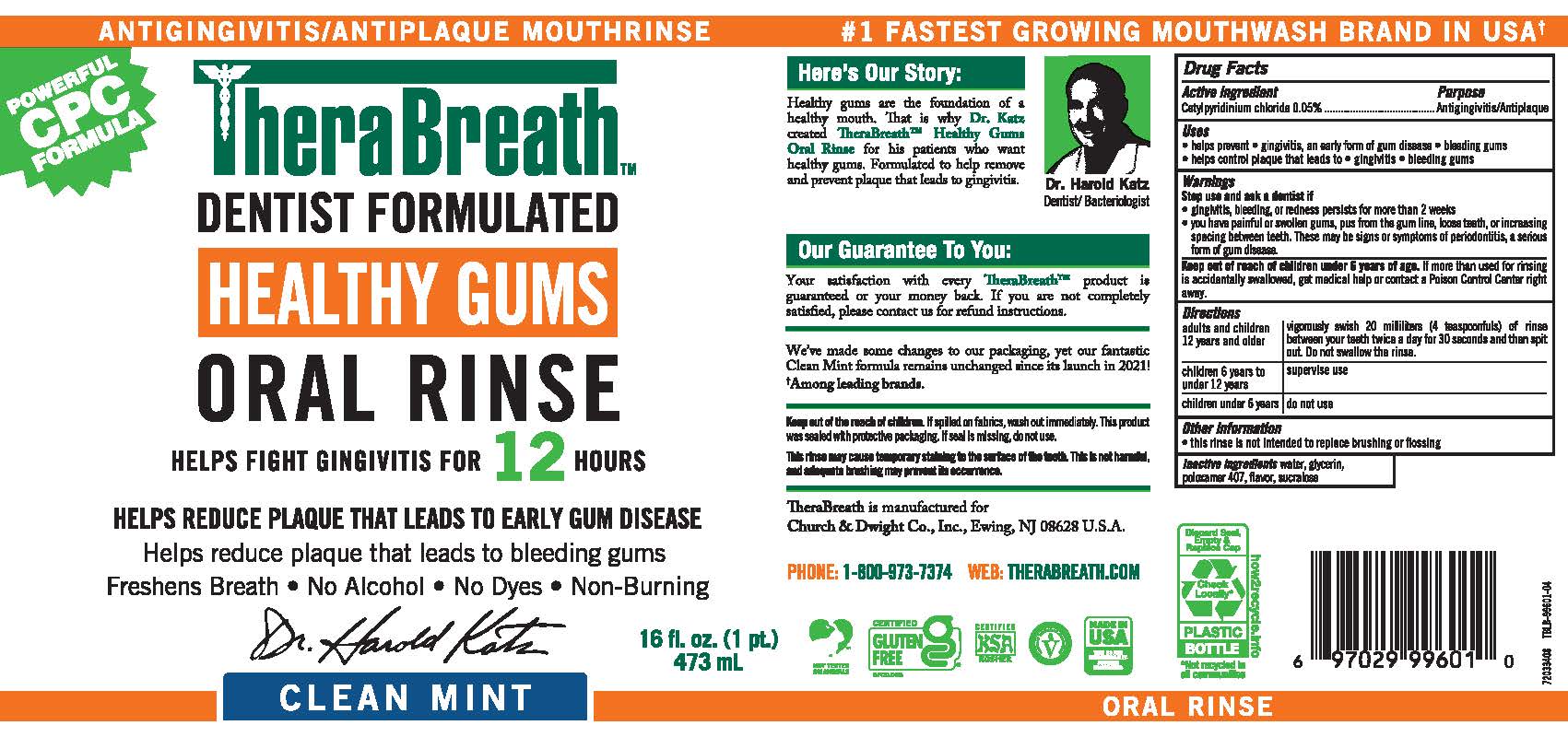 DRUG LABEL: TheraBreath Healthy Gums
NDC: 10237-258 | Form: RINSE
Manufacturer: Church & Dwight Co., Inc.
Category: otc | Type: HUMAN OTC DRUG LABEL
Date: 20251203

ACTIVE INGREDIENTS: CETYLPYRIDINIUM CHLORIDE 0.01 mg/20 mL
INACTIVE INGREDIENTS: WATER; GLYCERIN; POLOXAMER 407; SUCRALOSE

TheraBreath™Healthy Gums

Drug Facts

Active Ingredients

Cetylpyridinium Chloride 0.05%

Purpose

Antigingivitis/Antiplaque

Uses

- Helps prevent • gingivitis, an early form of gum disease • bleeding gums
- Helps control plaque that leads to • gingivitis • bleeding gums

Warnings

Stop use and ask a dentist if

- Gingivitis, bleeding, or redness persists for more than 2 weeks.
- You have painful or swollen gums, pus from the gum line, loose teeth, or increasing spacing between teeth. These may be signs or symptoms of periodontitis, a serious form of gum disease.

Keep out of reach of children under 6 years of age.If more than used for rinsing is accidentally swallowed, get medical help or contact a Poison Control Center right away.

Directions

Adults and Children 12 years and older | Vigorously swish 20 milliliters (4 teaspoonfuls) of rinse between your teeth twice a day for 30 seconds and then spit out. Do not swallow the rinse.
Children 6 years to under 12 years | Supervise use.
Children under 6 years | Do not use.

Other information

This rinse is not intended to replace brushing or flossing.

Inactive Ingredients

Water, Glycerin, Poloxamer 407, Flavor, Sucralose

PRINCIPAL DISPLAY PANEL - 473 mL Bottle Label

ANTIGINGIVITIS/ ANTIPLAQUE MOUTHRINSE

SAVE!
VALUE
SIZE

TheraBreath™

DENTIST FORMULATED

HEALTHY GUMS

ORAL RINSE

HELPS FIGHT GINGIVITIS FOR 24 HOURS*

HELPS REDUCE PLAQUE THAT LEADS TO GUM DISEASE

Reduces Occurrence of Bleeding Gums • Freshens Breath
No Alcohol • No Dyes • Non Burning

CLEAN MINT

33.8 fl. oz.
1 liter